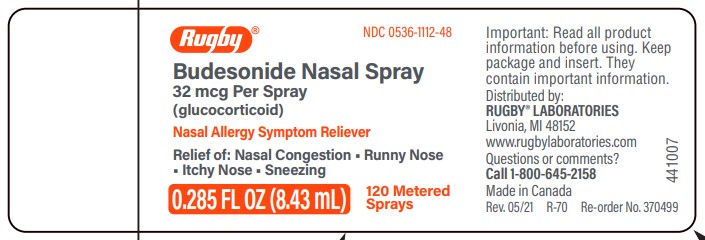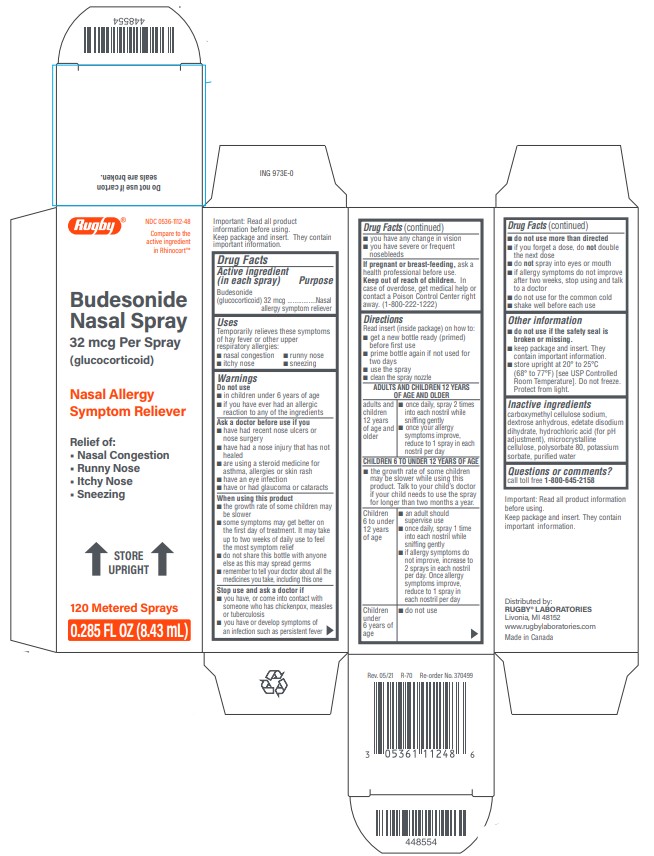 DRUG LABEL: Budesonide
NDC: 0536-1112 | Form: SPRAY, METERED
Manufacturer: Rugby Laboratories
Category: otc | Type: HUMAN OTC DRUG LABEL
Date: 20260227

ACTIVE INGREDIENTS: BUDESONIDE 32 ug/1 1
INACTIVE INGREDIENTS: EDETATE DISODIUM; CARBOXYMETHYLCELLULOSE SODIUM, UNSPECIFIED; MICROCRYSTALLINE CELLULOSE ; DEXTROSE, UNSPECIFIED FORM   ; POTASSIUM SORBATE; POLYSORBATE 80; HYDROCHLORIC ACID; WATER

Drug Facts

Active ingredient (in each spray)

Budesonide (glucocorticoid) 32 mcg

Purpose

Nasal allergy symptom reliever

Uses

Temporarily relieves these symptoms of hay fever or other upper respiratory allergies:

• nasal congestion • runny nose • itchy nose • sneezing

Warnings

Do not use

- in children under 6 years of age
- if you have ever had an allergic reaction to any of the ingredients

Ask a doctor before use if you

- have had recent nose ulcers or nose surgery
- have had a nose injury that has not healed
- are using a steroid medicine for asthma, allergies or skin rash
- have an eye infection
- have or had glaucoma or cataracts

When using this product

- the growth rate of some children may be slower
- some symptoms may get better on the first day of treatment. It may take up to two weeks of daily use to feel the most symptom relief.
- do not share this bottle with anyone else as this may spread germs
- remember to tell your doctor about all the medicines you take, including this one

Stop use and ask a doctor if

- you have, or come into contact with someone who has, chickenpox, measles or tuberculosis
- you have or develop symptoms of an infection such as persistent fever
- you have any change in vision
- you have severe or frequent nosebleeds

PREGNANCY OR BREAST FEEDING

If pregnant or breast-feeding, ask a health professional before use.

Keep out of reach of children.

In case of overdose, get medical help or contact a Poison Control Center right away (1-800-222-1222).

Directions

Read insert (inside package) on how to:

- get a new bottle ready (primed) before first use
- prime bottle again if not used for two days
- use the spray
- clean the spray nozzle

ADULTS AND CHILDREN 12 YEARS OF AGE AND OLDER
adults and children 12 years of age and older | - once daily, spray 2 times into each nostril while sniffing gently - once your allergy symptoms improve, reduce to 1 spray in each nostril per day
CHILDREN 6 TO UNDER 12 YEARS OF AGE
- the growth rate of some children may be slower while using this product. Talk to your child’s doctor if your child needs to use the spray for longer than two months a year
children 6 to under 12 years of age | - an adult should supervise use - once daily, spray 1 time into each nostril while sniffing gently - if allergy symptoms do not improve, increase to 2 sprays in each nostril per day. Once allergy symptoms improve, reduce to 1 spray in each nostril per day
children under 6 years of age | - do not use
- do not use more than directed
- if you forget a dose, do not double the next dose
- do not spray into eyes or mouth
- if allergy symptoms do not improve after two weeks, stop using and talk to a doctor
- do not use for the common cold
- shake well before each use

Other information

- do not use if the safety seal labeled "sealed for your protection" is broken or missing.
- keep package and insert. They contain important information.
- store at 20° to 25°C (68° to 77°F) [see USP Controlled Room Temperature]. Do not freeze. Protect from light.

Inactive ingredients

carboxymethyl cellulose sodium, dextrose anhydrous, edetate disodium dihydrate, hydrochloric acid (for pH adjustment), microcrystalline cellulose, polysorbate 80, potassium sorbate, purified water

Questions or comments?

call toll free 1-800-645-2158

Principal Display Panel - Carton 120ms

CARTON LABEL - PRINCIPAL DISPLAY PANEL - 32 mcg per spray

Rugby Laboratories NDC 0536-1112-48

Budesonide Nasal Spray

Allergy Spray

120 sprays

Relief of:

- Nasal Congestion
- Runny Nose
- Itchy Nose
- Sneezing

Principal Display Panel - Bottle 120ms

BOTTLE LABEL - PRINCIPAL DISPLAY PANEL - 32 mcg per spray

Rugby Laboratories NDC 0536-1112-48

Budesonide Nasal Spray

Allergy Spray

120 sprays